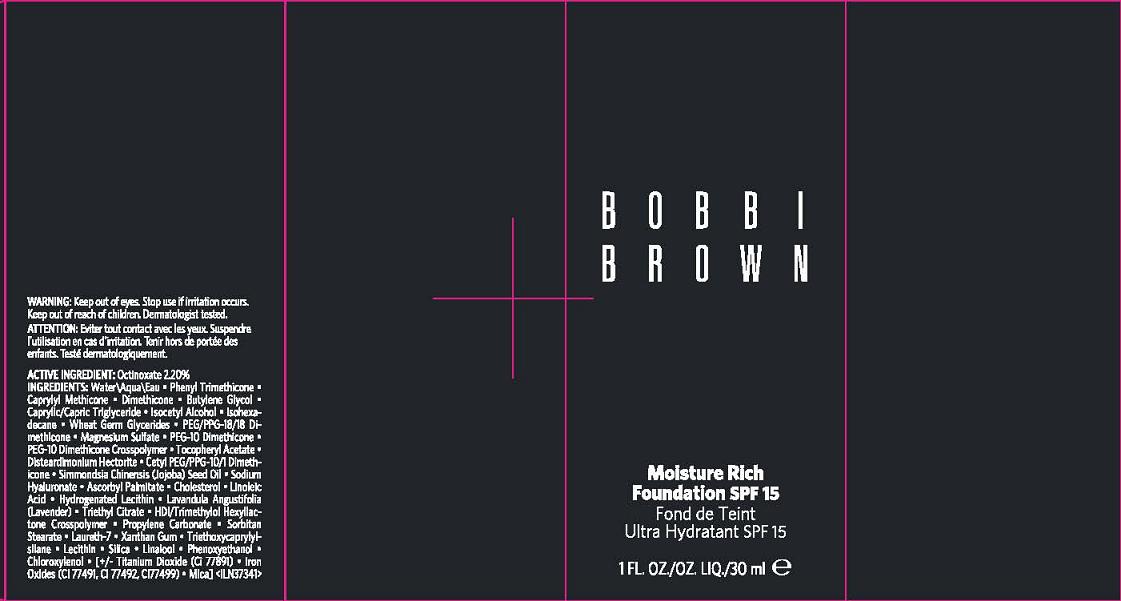 DRUG LABEL: MOISTURE RICH FOUNDATION
NDC: 64141-704 | Form: LIPSTICK
Manufacturer: Bobbi Brown Professional Cosmetics Inc.
Category: otc | Type: HUMAN OTC DRUG LABEL
Date: 20110923

ACTIVE INGREDIENTS: OCTINOXATE 2.2 mL/100 mL
INACTIVE INGREDIENTS: WATER; PHENYL TRIMETHICONE; DIMETHICONE; BUTYLENE GLYCOL; MEDIUM-CHAIN TRIGLYCERIDES; ISOCETYL ALCOHOL; ISOHEXADECANE; WHEAT GERM; MAGNESIUM SULFATE, UNSPECIFIED; ALPHA-TOCOPHEROL ACETATE; JOJOBA OIL; HYALURONATE SODIUM; ASCORBYL PALMITATE; CHOLESTEROL; LINOLEIC ACID; HYDROGENATED SOYBEAN LECITHIN; LAVANDULA ANGUSTIFOLIA FLOWER; TRIETHYL CITRATE; PROPYLENE CARBONATE; SORBITAN MONOSTEARATE; LAURETH-7; XANTHAN GUM; TRIETHOXYCAPRYLYLSILANE; LECITHIN, SOYBEAN; SILICON DIOXIDE; PHENOXYETHANOL; CHLOROXYLENOL; TITANIUM DIOXIDE; FERRIC OXIDE RED; MICA

ACTIVE INGREDIENT: OCTINOXATE 2.2%

INACTIVE INGREDIENT

INACTIVE INGREDIENTS: WATER\AQUA\EAU [] PHENYL TRIMETHICONE [] CAPRYLYL METHICONE [] DIMETHICONE [] BUTYLENE GLYCOL [] CAPRYLIC/CAPRIC TRIGLYCERIDE [] ISOCETYL ALCOHOL [] ISOHEXADECANE [] WHEAT GERM GLYCERIDES [] PEG/PPG-18/18 DIMETHICONE [] MAGNESIUM SULFATE [] PEG-10 DIMETHICONE [] PEG-10 DIMETHICONE CROSSPOLYMER [] TOCOPHERYL ACETATE [] DISTEARDIMONIUM HECTORITE [] CETYL PEG/PPG-10/1 DIMETHICONE [] SIMMONDSIA CHINENSIS (JOJOBA) SEED OIL [] SODIUM HYALURONATE [] ASCORBYL PALMITATE [] CHOLESTEROL [] LINOLEIC ACID [] HYDROGENATED LECITHIN [] LAVANDULA ANGUSTIFOLIA (LAVENDER) [] TRIETHYL CITRATE [] HDI/TRIMETHYLOL HEXYLLACTONE CROSSPOLYMER [] PROPYLENE CARBONATE [] SORBITAN STEARATE [] LAURETH-7 [] XANTHAN GUM [] TRIETHOXYCAPRYLYLSILANE [] LECITHIN [] SILICA [] LINALOOL [] PHENOXYETHANOL [] CHLOROXYLENOL [] [+/- TITANIUM DIOXIDE (CI 77891) [] IRON OXIDES (CI 77491, CI 77492, CI 77499) [] MICA]

WARNINGS

WARNING: KEEP OUT OF EYES. STOP USE IF IRRITATION OCCURS. KEEP OUT OF REACH OF CHILDREN

PACKAGE LABEL

PRINCIPAL DISPLAY PANEL:

BOBBI BROWN

MOISTURE RICH FOUNDATION

SPF 15

30 ML/ 1 FL OZ LIQ

DISTR BOBBI BROWN COSMETICS INC

NEW YORK, NY 10022